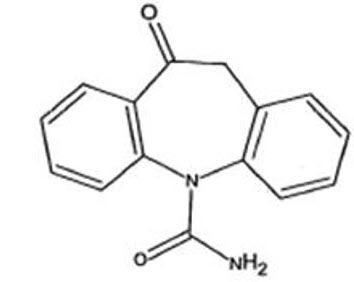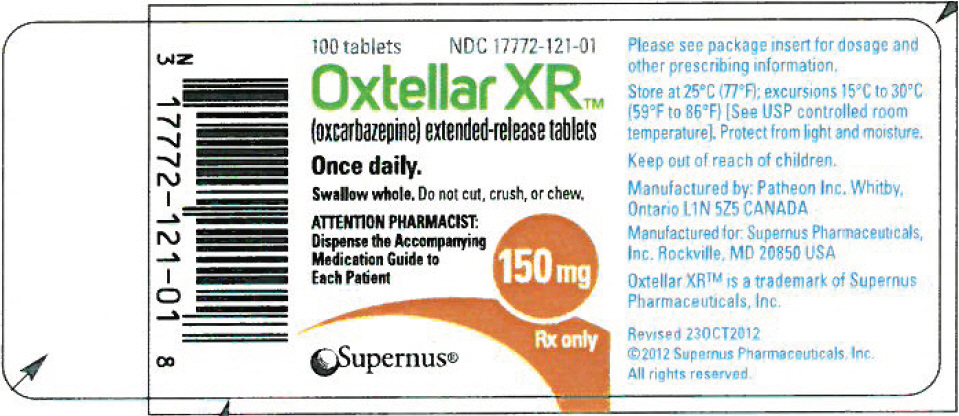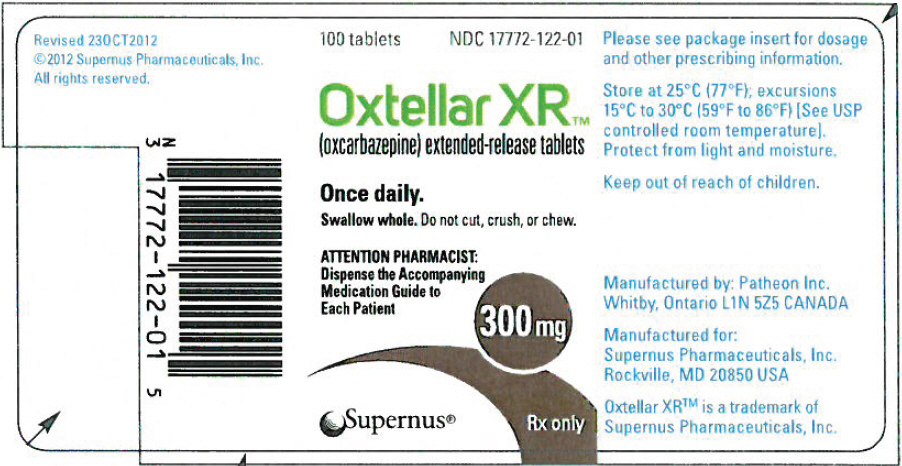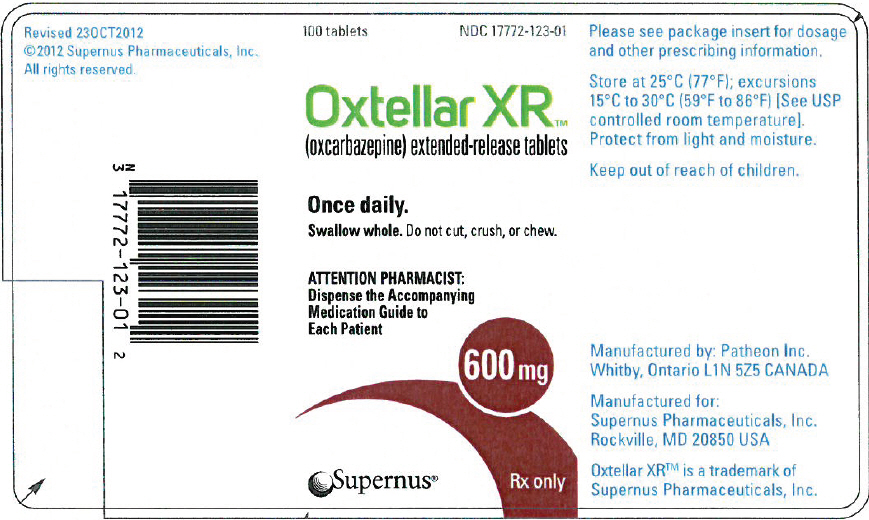 DRUG LABEL: OXTELLAR XR
NDC: 17772-122 | Form: TABLET
Manufacturer: Supernus Pharmaceuticals, Inc.
Category: prescription | Type: HUMAN PRESCRIPTION DRUG LABEL
Date: 20251022

ACTIVE INGREDIENTS: OXCARBAZEPINE 300 mg/1 1
INACTIVE INGREDIENTS: METHACRYLIC ACID AND ETHYL ACRYLATE COPOLYMER; MICROCRYSTALLINE CELLULOSE; POLYETHYLENE GLYCOL 2000; POLYVINYL ALCOHOL, UNSPECIFIED; POVIDONE, UNSPECIFIED; SODIUM LAURYL SULFATE; TALC; TITANIUM DIOXIDE; HYPROMELLOSE, UNSPECIFIED; SILICON DIOXIDE; FERRIC OXIDE YELLOW; FERRIC OXIDE RED; FERROSOFERRIC OXIDE; MAGNESIUM STEARATE

HIGHLIGHTS OF PRESCRIBING INFORMATION

These highlights do not include all the information needed to use OXTELLAR XR® safely and effectively. See full prescribing information for OXTELLAR XR®.
OXTELLAR XR® (oxcarbazepine) extended-release tablets, for oral use
Initial U.S. Approval: 2000

1 INDICATIONS AND USAGE

Oxtellar XR® is indicated for the treatment of partial-onset seizures in patients 6 years of age and older. (1)

2 DOSAGE AND ADMINISTRATION

- Adult Patients: The recommended initial dosage is 600 mg once per day. Increase the dosage in weekly increments of 600 mg once per day, based on clinical response and tolerability, to a recommended maintenance dosage of 1200 mg to 2400 mg once per day. (2.2)
- In adult patients with a creatinine clearance <30 mL/min, initiate at one-half the usual starting dosage and increase slowly. (2.3)
- Pediatric Patients: The recommended dosage is based on body weight and is administered orally once per day. Increase the dosage in weekly intervals based on clinical response and tolerability, to the recommended dosage. (2.2)
- Geriatric Patients: Start at lower dosage (300 mg or 450 mg/day) and increase slowly. (2.4)
- In conversion of oxcarbazepine immediate-release to Oxtellar XR®, higher dosages of Oxtellar XR may be necessary. (2.7, 12.3)

3 DOSAGE FORMS AND STRENGTHS

Extended-release tablets:150 mg, 300 mg and 600 mg (3)

4 CONTRAINDICATIONS

Known hypersensitivity to oxcarbazepine, any of the components of Oxtellar XR, or to eslicarbazepine acetate. (4)

5 WARNINGS AND PRECAUTIONS

- Hyponatremia:Monitor sodium as recommended. (5.1)
- Cross Hypersensitivity Reaction to Carbamazepine:Discontinue immediately if hypersensitivity occurs. (5.3)
- Serious Dermatological Reactions:Discontinue if observed. (5.4)
- Suicidal Behavior and Ideation:Monitor for symptoms. (5.5)
- Withdrawal ofOxtellar XR®:Withdrawal gradually. (5.6)
- Drug Reaction with Eosinophilia and Systemic symptoms (DRESS)/Multi-Organ Hypersensitivity:Discontinue if suspected. (5.7)
- Hematologic Reactions:Discontinue if suspected. (5.8)
- Risk of Seizure Aggravation:Discontinue if occurs. (5.10)

6 ADVERSE REACTIONS

Most commonly observed (≥5% and more frequent than placebo) adverse reactions in adults were dizziness, somnolence, headache, balance disorder, tremor, vomiting, diplopia, asthenia, and fatigue. (6.1)

Adverse reactions in pediatric patients are similar to those seen in adult patients.

To report SUSPECTED ADVERSE REACTIONS, contact Supernus, Inc. at (1-866-398-0833) or contact FDA at 1-800-FDA-1088 or www.fda.gov/medwatch

7 DRUG INTERACTIONS

- Phenytoin, Carbamazepine, and Phenobarbital:Coadministration decreased blood levels of an active metabolite of Oxtellar XR: Greater dosage of Oxtellar XR may be required. (2.5, 7.2)
- Oral Contraceptives: Advise patients that Oxtellar XR may decrease the effectiveness of hormonal contraceptives. Additional non-hormonal forms of contraception are recommended. (7.3)

8 USE IN SPECIFIC POPULATIONS

- Pregnancy:May cause fetal harm. (5.9, 8.1)
- Severe Hepatic Impairment:Not recommended. (8.7)

FULL PRESCRIBING INFORMATION

1 INDICATIONS AND USAGE

Oxtellar XR is indicated for the treatment of partial-onset seizures in patients 6 years of age and older.

2 DOSAGE AND ADMINISTRATION

2.1 Important Administration Instructions

Administer Oxtellar XR as a single daily dose taken on an empty stomach (at least 1 hour before or at least 2 hours after meals) [see Clinical Pharmacology (12.3)] . If Oxtellar XR is taken with food, adverse reactions are more likely to occur because of increased peak levels [see Clinical Pharmacology (12.3)].

Swallow Oxtellar XR tablets whole. Do not cut, crush, or chew the tablets. For ease of swallowing in pediatric patients or patients with difficulty swallowing, achieve daily dosages with multiples of appropriate lower strength tablets (e.g., 150 mg tablets).

2.2 General Dosing Recommendations

Monotherapy or Adjunctive Therapy

Adult Patients

Initiate treatment at a dosage of 600 mg/day given orally once daily for one week. Subsequent dosage increases can be made at weekly intervals in 600 mg/day increments to achieve the recommended daily dosage.

The recommended daily dosage of Oxtellar XR is 1200 mg to 2400 mg/day, given once daily. The dosage of 2400 mg/day showed slightly greater efficacy than 1200 mg/day, but was associated with an increase in adverse reactions [see Adverse Reactions (6.1)and Clinical Studies (14.1)].

Dosage adjustment is recommended with concomitant use of strong CYP3A4 enzyme inducers or UGT inducers, which include certain antiepileptic drugs (AEDs) [see Drug Interactions (7.1, 7.2)].

Pediatric Patients (6 to Less than 17 Years of Age)

In pediatric patients 6 to less than 17 years of age, initiate treatment at a daily dosage of 8 mg/kg to 10 mg/kg orally once daily, not to exceed 600 mg per day in the first week.

Subsequent dosage increases can be made at weekly intervals in 8 mg/kg to 10 mg/kg increments once daily, not to exceed 600 mg, to achieve the target daily dosage. The target maintenance dosage, achieved over two to three weeks, is displayed in Table 1.

Table 1: Target Daily Dosage in Pediatric Patients (6 to Less Than 17 Years of Age)
Weight | Target Daily Dosage
20 kg to 29 kg | 900 mg/day
29.1 kg to 39 kg | 1200 mg/day
Greater than 39 kg | 1800 mg/day

Dosage adjustment is recommended with concomitant use of strong CYP3A4 enzyme inducers or UGT inducers, which include certain antiepileptic drugs (AEDs) [see Drug Interactions (7.1, 7.2))].

2.3 Dosage Modifications in Adult Patients with Renal Impairment

In adult patients with severe renal impairment (creatinine clearance less than 30 mL/minute), initiate Oxtellar XR at one-half the usual starting dosage (300 mg/day). Subsequent dosage increases can be made at weekly intervals in increments of 300 mg to 450 mg/day to achieve the desired clinical response [see Use in Specific Populations (8.6)].

2.4 Dosage Modifications in Geriatric Patients

In geriatric patients, consider starting at a lower dosage (300 mg or 450 mg/day). Subsequent dosage increases can be made at weekly intervals in increments of 300 mg to 450 mg/day to achieve the desired clinical effect [see Use in Specific Populations (8.5)].

2.5 Dosage Modification with Concomitant Use of Strong CYP3A4 Enzyme Inducers or UGT Enzyme Inducers

Strong CYP3A4 inducers, including enzyme-inducing antiepileptic drugs such as carbamazepine, phenobarbital, and phenytoin, and UGT inducers (e.g., rifampin) decrease exposure to 10-monohydroxy derivative (MHD), the active metabolite [see Drug Interactions (7.2)and Clinical Pharmacology (12.3)] . Dosage adjustment of Oxtellar XR may be required after initiation, dosage modification, or discontinuation of such inducers. Dosage increases of Oxtellar XR may be necessary with concomitant use. Consider initiating at 900 mg once daily for adults and 12 to 15 mg/kg orally once daily (not to exceed 900 mg per day in the first week) in pediatric patients.

2.6 Withdrawal of AEDs

As with most antiepileptic drugs, Oxtellar XR should be withdrawn gradually because of the risk of increased seizure frequency and status epilepticus [see Warnings and Precautions (5.6)].

2.7 Conversion from Immediate-Release Oxcarbazepine to Oxtellar XR

In conversion of oxcarbazepine immediate-release to Oxtellar XR, higher dosages of Oxtellar XR may be necessary [see Clinical Pharmacology (12.3)].

3 DOSAGE FORMS AND STRENGTHS

Extended-release tablets:

- 150 mg: yellow modified-oval shaped with "150" printed on one side
- 300 mg: brown modified-oval shaped with "300" printed on one side
- 600 mg: brownish red modified-oval shaped with "600" printed on one side

4 CONTRAINDICATIONS

Oxtellar XR is contraindicated in patients with a known hypersensitivity to oxcarbazepine, to any of the components of Oxtellar XR, or to eslicarbazepine acetate. Reactions have included anaphylaxis and angioedema [see Warnings and Precautions (5.2, 5.3)].

5 WARNINGS AND PRECAUTIONS

5.1 Hyponatremia

Clinically significant hyponatremia (sodium <125 mmol/L) may develop during Oxtellar XR use. Serum sodium levels less than 125 mmol/L have occurred in immediate-release oxcarbazepine-treated patients generally in the first three months of treatment. However, clinically significant hyponatremia may develop more than a year after initiating therapy.

Most immediate-release oxcarbazepine-treated patients who developed hyponatremia were asymptomatic in clinical trials. However, some of these patients had their dosage reduced, discontinued, or had their fluid intake restricted for hyponatremia. Serum sodium levels returned toward normal when the dosage was reduced or discontinued, or when the patient was treated conservatively (e.g., fluid restriction). Cases of symptomatic hyponatremia and syndrome of inappropriate antidiuretic hormone secretion (SIADH) have been reported during post-marketing use of immediate-release oxcarbazepine.

Among treated patients in a controlled trial of adjunctive therapy with Oxtellar XR in 366 adults with complex partial seizures, 1 patient receiving 2400 mg experienced a severe reduction in serum sodium (117 mEq/L) requiring discontinuation from treatment, while 2 other patients receiving 1200 mg experienced serum sodium concentrations low enough (125 and 126 mEq/L) to require discontinuation from treatment. The overall incidence of clinically significant hyponatremia in patients treated with Oxtellar XR was 1.2%, although slight shifts in serum sodium concentrations from Normal to Low (<135 mEq/L) were observed for the 2400 mg (6.5%) and 1200 mg (9.8%) groups compared to placebo (1.7%).

Measure serum sodium concentrations if patients develop symptoms of hyponatremia (e.g., nausea, malaise, headache, lethargy, confusion, obtunded consciousness, or increase in seizure frequency or severity). Consider measurement of serum sodium concentrations during treatment with Oxtellar XR, particularly if the patient receives concomitant medications known to decrease serum sodium levels (for example, drugs associated with inappropriate ADH secretion).

5.2 Anaphylactic Reactions and Angioedema

Rare cases of anaphylaxis and angioedema involving the larynx, glottis, lips and eyelids have been reported in patients after taking the first or subsequent doses of immediate-release oxcarbazepine. Angioedema associated with laryngeal edema can be fatal. If a patient develops any of these reactions after treatment with Oxtellar XR, discontinue the drug and initiate an alternative treatment. Do not rechallenge these patients with Oxtellar XR.

5.3 Cross Hypersensitivity Reaction to Carbamazepine

Approximately 25% to 30% of patients who have had hypersensitivity reactions to carbamazepine will experience hypersensitivity reactions with Oxtellar XR. For this reason, patients should be specifically questioned about any prior experience with carbamazepine, and patients with a history of hypersensitivity reactions to carbamazepine should ordinarily be treated with Oxtellar XR only if the potential benefit justifies the potential risk. Discontinue Oxtellar XR immediately if signs or symptoms of hypersensitivity develop [see Warnings and Precautions (5.2, 5.7)].

5.4 Serious Dermatological Reactions

Serious dermatological reactions, including Stevens-Johnson syndrome (SJS) and toxic epidermal necrolysis (TEN), have occurred in both children and adults treated with immediate-release oxcarbazepine use. The median time of onset for reported cases was 19 days. Such serious skin reactions may be life threatening, and some patients have required hospitalization with very rare reports of fatal outcome. Recurrence of the serious skin reactions following rechallenge with immediate-release oxcarbazepine has also been reported.

The reporting rate of TEN and SJS associated with immediate-release oxcarbazepine use, which is generally accepted to be an underestimate due to underreporting, exceeds the background incidence rate estimates by a factor of 3- to 10-fold. Estimates of the background incidence rate for these serious skin reactions in the general population range between 0.5 to 6 cases per million-person years. Therefore, if a patient develops a skin reaction while taking Oxtellar XR, consider discontinuing Oxtellar XR use and prescribing another AED.

Association with HLA-B*1502

Patients carrying the HLA-B*1502 allele may be at increased risk for SJS/TEN with Oxtellar XR treatment.

Human Leukocyte Antigen (HLA) allele B*1502 increases the risk for developing SJS/TEN in patients treated with carbamazepine. The chemical structures of immediate-release oxcarbazepine and Oxtellar XR are similar to that of carbamazepine. Available clinical evidence, and data from nonclinical studies showing a direct interaction between immediate-release oxcarbazepine and HLA-B*1502 protein, suggest that the HLA-B*1502 allele may also increase the risk for SJS/TEN with Oxtellar XR.

The frequency of HLA-B*1502 allele ranges from 2 to 12% in Han Chinese populations, is about 8% in Thai populations, and above 15% in the Philippines and in some Malaysian populations. Allele frequencies up to about 2% and 6% have been reported in Korea and India, respectively. The frequency of the HLA-B*1502 allele is negligible in people from European descent, several African populations, indigenous peoples of the Americas, Hispanic populations, and in Japanese (<1%).

Testing for the presence of the HLA-B*1502 allele should be considered in patients with ancestry in genetically at-risk populations, prior to initiating treatment with Oxtellar XR. The use of Oxtellar XR should be avoided in patients positive for HLA-B*1502 unless the benefits clearly outweigh the risks. Consideration should also be given to avoid the use of other drugs associated with SJS/TEN in HLA-B*1502 positive patients, when alternative therapies are otherwise equally acceptable. Screening is not generally recommended in patients from populations in which the prevalence of HLA-B*1502 is low, or in current Oxtellar XR users, as the risk of SJS/TEN is largely confined to the first few months of therapy, regardless of HLA-B*1502 status.

The use of HLA-B*1502 genotyping has important limitations and must never substitute for appropriate clinical vigilance and patient management. The role of other possible factors in the development of, and morbidity from, SJS/TEN, such as antiepileptic drug (AED) dosage, compliance, concomitant medications, comorbidities, and the level of dermatologic monitoring have not been well characterized.

5.5 Suicidal Behavior and Ideation

Antiepileptic drugs (AEDs), including Oxtellar XR, increase the risk of suicidal thoughts or behavior in patients taking these drugs for any indication. Monitor patients treated with any AED for any indication for the emergence or worsening of depression, suicidal thoughts or behavior, and/or any unusual changes in mood or behavior.

Pooled analyses of 199 placebo-controlled clinical trials (mono- and adjunctive therapy) of 11 different AEDs showed that patients randomized to one of the AEDs had approximately twice the risk (adjusted Relative Risk 1.8, 95% CI:1.2, 2.7) of suicidal thinking or behavior compared to patients randomized to placebo. In these trials, which had a median treatment duration of 12 weeks, the estimated incidence rate of suicidal behavior or ideation among 27,863 AED-treated patients was 0.43%, compared to 0.24% among 16,029 placebo-treated patients, representing an increase of approximately one case of suicidal thinking or behavior for every 530 patients treated. There were four suicides in drug-treated patients in the trials and none in placebo-treated patients, but the number is too small to allow any conclusion about drug effect on suicide.

The increased risk of suicidal thoughts or behavior with AEDs was observed as early as one week after starting drug treatment with AEDs and persisted for the duration of treatment assessed. Because most trials included in the analysis did not extend beyond 24 weeks, the risk of suicidal thoughts or behavior beyond 24 weeks could not be assessed.

The risk of suicidal thoughts or behavior was generally consistent among drugs in the data analyzed. The finding of increased risk with AEDs of varying mechanisms of action and across a range of indications suggests that the risk applies to all AEDs used for any indication. The risk did not vary substantially by age (5-100 years) in the clinical trials analyzed. Table 2 shows absolute and relative risk by indication for all evaluated AEDs.

Table 2: Risk by Indication for Antiepileptic Drugs in the Pooled Analysis
Indication | Placebo Patients with Events per 1000 Patients | Drug Patients with Events per 1000 Patients | Relative Risk: Incidence of Events in Drug Patients/Incidence in Placebo Patients | Risk Difference: Additional Drug Patients with Events per 1000 Patients
Epilepsy | 1.0 | 3.4 | 3.5 | 2.4
Psychiatric | 5.7 | 8.5 | 1.5 | 2.9
Other | 1.0 | 1.8 | 1.9 | 0.9
Total | 2.4 | 4.3 | 1.8 | 1.9

The relative risk for suicidal thoughts or behavior was higher in clinical trials for epilepsy than in clinical trials for psychiatric or other conditions, but the absolute risk differences were similar for the epilepsy and psychiatric indications.

Anyone considering prescribing Oxtellar XR or any other AED must balance the risk of suicidal thoughts or behavior with the risk of untreated illness. Epilepsy and many other illnesses for which AEDs are prescribed are themselves associated with morbidity and mortality and an increased risk of suicidal thoughts and behavior. Should suicidal thoughts and behavior emerge during Oxtellar XR treatment, the prescriber needs to consider whether the emergence of these symptoms in any given patient may be related to the illness being treated.

5.6 Withdrawal of AEDs

As with most AEDs, Oxtellar XR should be withdrawn gradually because of the risk of increased seizure frequency and status epilepticus. But if withdrawal is needed because of a serious adverse event, rapid discontinuation can be considered.

5.7 Drug Reaction with Eosinophilia and Systemic Symptoms (DRESS)/Multi-Organ Hypersensitivity

Drug Reaction with Eosinophilia and Systemic Symptoms (DRESS), also known as multi-organ hypersensitivity, has occurred with immediate-release oxcarbazepine. Some of these events have been fatal or life-threatening. DRESS typically, although not exclusively, presents with fever, rash, lymphadenopathy, and/or facial swelling, in associated with other organ system involvement, such as hepatitis, nephritis, hematologic abnormalities, myocaraditis, or myositis sometimes resembling an acute viral infection. Eosinophilia is often present. This disorder is variable in its expression, and other organ systems not noted here may be involved. It is important to note that early manifestatios of hypersensitivity (e.g., fever, lymphadenopathy) may be present even though rash is not evident. Oxtellar XR should be discontinued if an alternative etiology for the signs and symptoms cannot be established.

5.8 Hematologic Reactions

Rare reports of pancytopenia, agranulocytosis, and leukopenia have been seen in patients treated with immediate-release oxcarbazepine during post-marketing experience. Discontinuation of Oxtellar XR should be considered if any evidence of these hematologic reactions develops.

5.9 Risk of Seizures in the Pregnant Patient

Due to physiological changes during pregnancy, plasma concentrations of the active metabolite of oxcarbazepine, the 10-monohydroxy derivative (MHD), may gradually decrease throughout pregnancy. Monitor patients carefully during pregnancy and through the postpartum period because MHD concentrations may increase after delivery.

5.10 Risk of Seizure Aggravation

Exacerbation of or new onset primary generalized seizures has been reported with immediate-release oxcarbazepine. The risk of aggravation of primary generalized seizures is seen especially in children but may also occur in adults. In case of seizure aggravation, Oxtellar XR should be discontinued.

6 ADVERSE REACTIONS

The following serious adverse reactions are described in other sections of the labeling:

- Hyponatremia [see Warnings and Precautions (5.1)]
- Anaphylactic Reactions and Angioedema [see Warnings and Precautions (5.2)]
- Cross Hypersensitivity Reaction to Carbamazepine [see Warnings and Precautions (5.3)]
- Serious Dermatological Reactions [see Warnings and Precautions (5.4)]
- Suicidal Behavior and Ideation [see Warnings and Precautions (5.5)]
- Withdrawal of AEDs [see Warnings and Precautions (5.6)]
- Drug Reaction with Eosinophilia and Systemic Symptoms (DRESS)/Multi-Organ Hypersensitivity [see Warnings and Precautions (5.7)]
- Hematologic Reactions [see Warnings and Precautions (5.8)]
- Risk of Seizures in the Pregnant Patient [see Warnings and Precautions (5.9)]

6.1 Clinical Trials Experience

Because clinical trials are conducted under widely varying conditions, adverse reaction rates observed in the clinical trials of a drug cannot be directly compared to rates in the clinical trials of another drug and may not reflect the rates observed in clinical practice.

The safety data presented below are from 384 patients with partial-onset seizures who received Oxtellar XR (366 adults and 18 pediatric patients) with concomitant AEDs.

In addition, safety data presented below are from a total of 2288 patients with seizure disorders treated with immediate-release oxcarbazepine; 1832 were adults and 456 were pediatric patients.

Most Common Adverse Reactions Reported by Adult Patients Receiving Concomitant AEDs in Oxtellar XR Clinical Studies

Table 3 lists adverse reactions that occurred in at least 2% of adult patients with epilepsy treated with Oxtellar XR or placebo and concomitant AEDs and that were numerically more common in the patients treated with any dosage of Oxtellar XR than in patients receiving placebo.

Table 3: Adverse Reaction Incidence in a Controlled Clinical Study of Oxtellar XR with Concomitant AEDs in Adults [Reported by ≥ 2% of patients treated with Oxtellar XR and numerically more frequent than in the placebo group]
 | Oxtellar XR 2400 mg/day N=123 % | Oxtellar XR 1200 mg/day N=122 % | Placebo N=121 %
Any System / Any Term | 69 | 57 | 55
Nervous System Disorders
Dizziness | 41 | 20 | 15
Somnolence | 14 | 12 | 9
Headache | 15 | 8 | 7
Balance Disorder | 7 | 5 | 5
Tremor | 1 | 5 | 2
Nystagmus | 3 | 3 | 1
Ataxia | 1 | 3 | 1
Gastrointestinal Disorders
Vomiting | 15 | 6 | 9
Abdominal Pain Upper | 0 | 3 | 1
Dyspepsia | 0 | 3 | 1
Gastritis | 0 | 3 | 2
Eye Disorders
Diplopia | 13 | 10 | 4
Vision Blurred | 1 | 4 | 3
Visual Impairment | 1 | 3 | 0
General Disorders and Administration Site Conditions
Asthenia | 7 | 3 | 1
Fatigue | 3 | 6 | 1
Gait Disturbance | 0 | 3 | 1
Drug Intolerance | 2 | 0 | 0
Infections and Infestations
Nasopharyngitis | 0 | 3 | 0
Sinusitis | 0 | 3 | 2

The overall incidence of adverse reactions appeared to be dose related, particularly during the titration period. The most commonly observed (≥ 5%) adverse reactions seen in association with Oxtellar XR and more frequent than in placebo-treated patients were: dizziness, somnolence, headache, balance disorder, tremor, vomiting, diplopia, and asthenia.

Adverse Reactions Associated with Discontinuation of Oxtellar XR Treatment:Approximately 23.3% of the 366 adult patients receiving Oxtellar XR in clinical studies discontinued treatment because of an adverse reaction. The adverse reactions most commonly associated with discontinuation of Oxtellar XR (reported by ≥2%) were: dizziness (9.8%), vomiting (5.3%), nausea (3.7%), diplopia (3.2%), and somnolence (2.4%).

Adjunctive Therapy with Oxtellar XR in Pediatric Patients 6 to Less than 17 Years of Age Previously Treated with other AEDs

In a pharmacokinetic study in 18 pediatric patients (including patients 6 to less than 17 years of age) with partial-onset seizures treated with different dosages of Oxtellar XR, the observed adverse reactions seen in association with Oxtellar XR were similar to those seen in adults.

Most Common Adverse Reactions in Immediate-Release Oxcarbazepine Controlled Clinical Studies

Controlled Clinical Studies of Adjunctive Therapy with Immediate-Release Oxcarbazepine in Adults Previously Treated with other AEDs:Table 4 lists adverse reactions that occurred in at least 2% of adult patients with epilepsy treated with immediate-release oxcarbazepine or placebo with concomitant AEDs and that were numerically more common in the patients treated with any dosage of immediate-release oxcarbazepine than in placebo. As immediate-release oxcarbazepine and Oxtellar XR were not examined in the same trial, adverse event frequencies cannot be directly compared between the two formulations.

Table 4: Adverse Reaction Incidence in a Controlled Clinical Study of Immediate Release Oxcarbazepine with Concomitant AEDs in Adults [Events in at least 2% of patients treated with 2400mg/day of immediate-release oxcarbazepine and numerically more frequent than in the placebo group]
 | Immediate-Release Oxcarbazepine Dosage (mg/day) |  |  | Placebo N = 166 %
 | OXC 600 N = 163 % | OXC 1200 N = 171 % | OXC 2400 N = 126 % | Placebo N = 166 %
Body as a Whole
Fatigue | 15 | 12 | 15 | 7
Asthenia | 6 | 3 | 6 | 5
Edema Legs | 2 | 1 | 2 | 1
Weight Increase | 1 | 2 | 2 | 1
Feeling Abnormal | 0 | 1 | 2 | 0
Cardiovascular System
Hypotension | 0 | 1 | 2 | 0
Digestive System
Nausea | 15 | 25 | 29 | 10
Vomiting | 13 | 25 | 36 | 5
Pain Abdominal | 10 | 13 | 11 | 5
Diarrhea | 5 | 6 | 7 | 6
Dyspepsia | 5 | 5 | 6 | 2
Constipation | 2 | 2 | 6 | 4
Gastritis | 2 | 1 | 2 | 1
Metabolic and Nutritional Disorders
Hyponatremia | 3 | 1 | 2 | 1
Musculoskeletal System
Muscle Weakness | 1 | 2 | 2 | 0
Sprains and Strains | 0 | 2 | 2 | 1
Nervous System
Headache | 32 | 28 | 26 | 23
Dizziness | 36 | 32 | 49 | 13
Somnolence | 20 | 28 | 36 | 12
Ataxia | 9 | 17 | 31 | 5
Nystagmus | 7 | 20 | 26 | 5
Gait Abnormal | 5 | 10 | 17 | 1
Insomnia | 4 | 2 | 3 | 1
Tremor | 3 | 8 | 16 | 5
Nervousness | 2 | 4 | 2 | 1
Agitation | 1 | 1 | 2 | 1
Coordination Abnormal | 1 | 3 | 2 | 1
EEG Abnormal | 0 | 0 | 2 | 0
Speech Disorder | 1 | 1 | 3 | 0
Confusion | 1 | 1 | 2 | 1
Cranial Injury NOS | 1 | 0 | 2 | 1
Dysmetria | 1 | 2 | 3 | 0
Thinking Abnormal | 0 | 2 | 4 | 0
Respiratory System
Rhinitis | 2 | 4 | 5 | 4
Skin and Appendages
Acne | 1 | 2 | 2 | 0
Special Senses
Diplopia | 14 | 30 | 40 | 5
Vertigo | 6 | 12 | 15 | 2
Vision Abnormal | 6 | 14 | 13 | 4
Accommodation Abnormal | 0 | 0 | 2 | 0

Other Reactions Observed in Association with the Administration of Immediate-Release Oxcarbazepine

In the paragraphs that follow, the adverse reactions, other than those in the preceding tables or text, that occurred in a total of 565 children and 1574 adults exposed to immediate-release oxcarbazepine and that are reasonably likely to be related to drug use are presented. Events common in the population, events reflecting chronic illness and events likely to reflect concomitant illness are omitted particularly if minor. They are listed in order of decreasing frequency. Because the reports cite reactions observed in open-label and uncontrolled trials, the role of immediate-release oxcarbazepine in their causation cannot be reliably determined.

Body as a Whole:fever, malaise, pain chest precordial, rigors, weight decrease.

Cardiovascular System:bradycardia, cardiac failure, cerebral hemorrhage, hypertension, hypotension postural, palpitation, syncope, tachycardia.

Digestive System:appetite increased, blood in stool, cholelithiasis, colitis, duodenal ulcer, dysphagia, enteritis, eructation, esophagitis, flatulence, gastric ulcer, gingival bleeding, gum hyperplasia, hematemesis, hemorrhage rectum, hemorrhoids, hiccup, mouth dry, pain biliary, pain right hypochondrium, retching, sialoadenitis, stomatitis, stomatitis ulcerative.

Hematologic and Lymphatic System:thrombocytopenia.

Laboratory Abnormality:gamma-GT increased, hyperglycemia, hypocalcemia, hypoglycemia, hypokalemia, liver enzymes elevated, serum transaminase increased.

Musculoskeletal System:hypertonia muscle.

Nervous System:aggressive reaction, amnesia, anguish, anxiety, apathy, aphasia, aura, convulsions aggravated, delirium, delusion, depressed level of consciousness, dysphonia, dystonia, emotional lability, euphoria, extrapyramidal disorder, feeling drunk, hemiplegia, hyperkinesia, hyperreflexia, hypoesthesia, hypokinesia, hyporeflexia, hypotonia, hysteria, libido decreased, libido increased, manic reaction, migraine, muscle contractions involuntary, nervousness, neuralgia, oculogyric crisis, panic disorder, paralysis, paroniria, personality disorder, psychosis, ptosis, stupor, tetany.

Respiratory System:asthma, bronchitis, coughing, dyspnea, epistaxis, laryngismus, pleurisy.

Skin and Appendages:acne, alopecia, angioedema, bruising, dermatitis contact, eczema, facial rash, flushing, folliculitis, heat rash, hot flushes, photosensitivity reaction, pruritus genital, psoriasis, purpura, rash erythematous, rash maculopapular, vitiligo, urticaria.

Special Senses:accommodation abnormal, cataract, conjunctival hemorrhage, edema eye, hemianopia, mydriasis, otitis externa, photophobia, scotoma, taste perversion, tinnitus, xerophthalmia.

Urogenital and Reproductive System:dysuria, hematuria, intermenstrual bleeding, leukorrhea, menorrhagia, micturition frequency, pain renal, pain urinary tract, polyuria, priapism, renal calculus, urinary tract infection.

Other:Systemic lupus erythematosus.

Laboratory Tests

Serum sodium levels below 125 mmol/L have been observed in patients treated with immediate-release oxcarbazepine [see Warnings and Precautions (5.1)]. Experience from clinical trials with immediate-release oxcarbazepine indicates that serum sodium levels return toward normal when the dosage is reduced or discontinued, or when the patient was treated conservatively (e.g., fluid restriction).

Laboratory data from clinical trials suggest that immediate-release oxcarbazepine use was associated with decreases in T4, without changes in T3 or TSH.

6.2 Postmarketing and Other Experience

The following adverse reactions have been observed in named patient programs or post-marketing experience with immediate-release oxcarbazepine or Oxtellar XR. Because these reactions are reported voluntarily from a population of uncertain size, it is not always possible to reliably estimate their frequency or establish a causal relationship to drug exposure.

Body as a Whole:multi-organ hypersensitivity disorders characterized by features such as rash, fever, lymphadenopathy, abnormal liver function tests, eosinophilia, and arthralgia [see Warnings and Precautions (5.7)]

Cardiovascular System:atrioventricular block

Digestive System:pancreatitis and/or lipase and/or amylase increase

Hematologic and Lymphatic Systems:aplastic anemia [see Warnings and Precautions (5.8)]

Immune System Disorders: anaphylaxis [see Warnings and Precautions (5.2)]

Metabolism and Nutrition Disorders: hypothyroidism and syndrome of inappropriate antidiuretic hormone secretion (SIADH)

Skin and Subcutaneous Tissue Disorders:erythema multiforme, Stevens-Johnson syndrome, toxic epidermal necrolysis [see Warnings and Precautions (5.4)] , Acute Generalized Exanthematous Pustulosis (AGEP)

Musculoskeletal, Connective Tissu,e and Bone Disorders: There have been reports of decreased bone mineral density, osteoporosis and fractures in patients on long-term therapy with immediate-release oxcarbazepine.

7 DRUG INTERACTIONS

7.1 Effect of Oxtellar XR on Other Drugs

It is recommended that the plasma levels of phenytoin be monitored during the period of Oxtellar XR titration and dosage modification [see Clinical Pharmacology (12.3)]. A decrease in the dosage of phenytoin may be required.

7.2 Effect of Other Drugs on Oxtellar XR

If Oxtellar XR and strong CYP3A4 inducers or UGT inducers (e.g., rifampin, carbamazepine, phenytoin and phenobarbital) are administered concurrently, it is recommended that the plasma levels of MHD be monitored during the period of Oxtellar XR titration [see Clinical Pharmacology (12.3)]. Dosage adjustment of Oxtellar XR may be required after initiation, dosage modification, or discontinuation of such inducers [see Dosage and Administration (2.5)].

7.3 Hormonal Contraceptives

Concurrent use of immediate-release oxcarbazepine with hormonal contraceptives may render these contraceptives less effective [see Clinical Pharmacology (12.3)]. Studies with other oral or implant contraceptives have not been conducted.

8 USE IN SPECIFIC POPULATIONS

8.1 Pregnancy

Pregnancy Exposure Registry

There is a pregnancy exposure registry that monitors pregnancy outcomes in women exposed to AEDs, such as Oxtellar XR, during pregnancy. Encourage women who are taking Oxtellar XR during pregnancy to enroll in the North American Antiepileptic Drug (NAAED Pregnancy Registry) by calling 1-888-233-2334 or visiting http://www.aedpregnancyregistry.org/.

Risk Summary

There are no adequate data on the developmental risks associated with the use of Oxtellar XR in pregnant women; however, Oxtellar XR is closely related structurally to carbamazepine, which is considered to be teratogenic in humans. Data on a limited number of pregnancies from pregnancy registries suggest that oxcarbazepine monotherapy use is associated with congenital malformations (e.g., craniofacial defects such as oral clefts, and cardiac malformations such as ventricular septal defects). Increased incidences of fetal structural abnormalities and other manifestations of developmental toxicity (embryolethality, growth retardation) were observed in the offspring of animals treated with either oxcarbazepine or its active 10-hydroxy metabolite (MHD) during pregnancy at doses similar to the maximum recommended human dose (MRHD).

In the U.S. general population, the estimated background risk of major birth defects and miscarriage in clinically recognized pregnancies is 2-4% and 15-20%, respectively. The background risk of major birth defects and miscarriage for the indicated population is unknown.

Clinical Considerations

An increase in seizure frequency may occur during pregnancy because of altered levels of the active metabolite of oxcarbazepine. Monitor patients carefully during pregnancy and through the postpartum period [see Warnings and Precautions (5.9)]

Data

Human Data

Data from published registries have reported craniofacial defects such as oral clefts and cardiac malformations such as ventricular septal defects in children with prenatal oxcarbazepine exposure.

Animal Data

When pregnant rats were given oxcarbazepine (30, 300, or 1000 mg/kg/day) orally throughout the period of organogenesis, increased incidences of fetal malformations (craniofacial, cardiovascular, and skeletal) and variations were observed at the intermediate and high doses (approximately 1.2 and 4 times, respectively, the MRHD on a mg/m^2basis). Increased embryofetal death and decreased fetal body weights were seen at the high dose. Doses ≥ 300 mg/kg were also maternally toxic (decreased body weight gain, clinical signs), but there is no evidence to suggest that teratogenicity was secondary to the maternal effects.

In a study in which pregnant rabbits were orally administered MHD (20, 100, or 200 mg/kg/day) during organogenesis, embryofetal mortality was increased at the highest dose (1.5 times the MRHD on a mg/m^2basis). This dose produced only minimal maternal toxicity.

In a study in which female rats were dosed orally with oxcarbazepine (25, 50, or 150 mg/kg/day) during the latter part of gestation and throughout the lactation period, a persistent reduction in body weights and altered behavior (decreased activity) were observed in offspring exposed to the highest dose (0.6 times the MRHD on a mg/m^2basis). Oral administration of MHD (25, 75, or 250 mg/kg/day) to rats during gestation and lactation resulted in a persistent reduction in offspring weights at the highest dose (equivalent to the MRHD on a mg/m^2basis).

8.2 Lactation

Risk Summary

Oxcarbazepine and its active metabolite (MHD) are present in human milk after oxcarbazepine administration. The effects of oxcarbazepine and its active metabolite (MHD) on the breastfed infant or on milk production are unknown. The developmental and health benefits of breastfeeding should be considered along with the mother's clinical need for Oxtellar XR and any potential adverse effects on the breastfed infant from Oxtellar XR or from the underlying maternal condition.

8.3 Females and Males of Reproductive Potential

Contraception

Use of Oxtellar XR with hormonal contraceptives containing ethinylestradiol or levonorgestrel is associated with decreased plasma concentrations of these hormones and may result in a failure of the therapeutic effect of the oral contraceptive drug. Advise women of reproductive potential taking Oxtellar XR who are using a contraceptive containing ethinylestradiol or levonorgestrel to use additional or alternative non-hormonal birth control [see Drug Interactions (7.3)and Clinical Pharmacology (12.3)].

8.4 Pediatric Use

The safety and effectiveness of Oxtellar XR in pediatric patients 6 years of age and older for the treatment of partial-onset seizures is supported by:

- An adequate and well-controlled safety and efficacy study of Oxtellar XR in adults that included pharmacokinetic sampling [see Clinical Studies (14.1)],
- A pharmacokinetic study of Oxtellar XR in pediatric patients, which included patients 6 to less than 17 years of age [see Clinical Pharmacology (12.3)],
- Safety and efficacy studies with the immediate-release formulation in adults and pediatric patients [see Clinical Studies (14.2)and Adverse Reactions (6.1)] .

Oxtellar XR®is not approved for pediatric patients less than 6 years of age because the size of the tablets are inappropriate for younger children.

8.5 Geriatric Use

Following administration of single (300 mg) and multiple (600 mg/day) doses of immediate-release oxcarbazepine to elderly volunteers (60-82 years of age), the maximum plasma concentrations and AUC values of MHD were 30%-60% higher than in younger volunteers (18-32 years of age). Comparisons of creatinine clearance in young and elderly volunteers indicate that the difference was due to age-related reductions in creatinine clearance. Consider starting at a lower dosage and lower titration [see Dosage and Administration (2.4)] . Close monitoring of sodium levels is required in elderly patients at risk for hyponatremia [see Warnings and Precautions (5.1)].

8.6 Renal Impairment

There is a linear correlation between creatinine clearance and the renal clearance of MHD [see Clinical Pharmacology (12.3)and Dosage and Administration (2.3)].

The pharmacokinetics of Oxtellar XR has not been evaluated in patients with renal impairment. In patients with severe renal impairment (creatinine clearance <30 mL/min) given immediate-release oxcarbazepine, the elimination half-life of MHD was prolonged with a corresponding two-fold increase in AUC [see Clinical Pharmacology (12.3)]. In these patients initiate Oxtellar XR at a lower starting dosage and increase, if necessary, at a slower than usual rate until the desired clinical response is achieved [see Dosage and Administration (2.3)] .

In patients with end-stage renal disease on dialysis, it is recommended that immediate-release oxcarbazepine be used instead of Oxtellar XR.

8.7 Hepatic Impairment

The pharmacokinetics of oxcarbazepine and MHD has not been evaluated in severe hepatic impairment, and therefore is not recommended in these patients [see Clinical Pharmacology (12.3)].

9 DRUG ABUSE AND DEPENDENCE

9.2 Abuse

The abuse potential of Oxtellar XR has not been evaluated in human studies. Oxtellar XR is not habit forming, and is not expected to encourage abuse.

9.3 Dependence

Intragastric injections of oxcarbazepine to four cynomolgus monkeys demonstrated no signs of physical dependence as measured by the desire to self-administer oxcarbazepine by lever pressing activity.

10 OVERDOSAGE

10.1 Human Overdose Experience

Isolated cases of overdose with immediate-release oxcarbazepine have been reported. The maximum dose taken was approximately 48,000 mg. All patients recovered with symptomatic treatment. Nausea, vomiting, somnolence, aggression, agitation, hypotension, and tremor each occurred in more than one patient. Coma, confusional state, convulsion, dyscoordination, depressed level of consciousness, diplopia, dizziness, dyskinesia, dyspnea, QT prolongation, headache, miosis, nystagmus, overdose, decreased urine output, and blurred vision also occurred.

10.2 Treatment and Management

There is no specific antidote for Oxtellar XR overdose. Administer symptomatic and supportive treatment as appropriate. Options include removal of the drug by gastric lavage and/or inactivation by administering activated charcoal.

11 DESCRIPTION

Oxtellar XR is an antiepileptic drug (AED). Oxtellar XR extended-release tablets contain oxcarbazepine for once-a-day oral administration. Oxcarbazepine is 10,11-Dihydro-10-oxo-5H-dibenz[b,f]-azepine-5-carboxamide, and its structural formula is

Oxcarbazepine is off-white to yellow crystalline powder.

Oxcarbazepine is sparingly soluble in chloroform (30-100 g/L). In aqueous media over pH range 1 to 8, oxcarbazepine is practically insoluble and its solubility is 40 mg/L (0.04 g/L) at pH 7.0, 25°C. The molecular formula is C15H12N2O2and its molecular weight is 252.27.

Oxtellar XR tablets contain the following inactive ingredients: colloidal silicon dioxide, hypromellose, yellow iron oxide (150 mg, 300 mg tablets only), red iron oxide (300 mg, 600 mg tablets only), black iron oxide (300 mg tablet only), magnesium stearate, methacrylic acid copolymer, microcrystalline cellulose, polyethylene glycol, polyvinyl alcohol, povidone, sodium lauryl sulfate, talc, and titanium dioxide. Each tablet is printed on one side with edible black ink.

12 CLINICAL PHARMACOLOGY

12.1 Mechanism of Action

The pharmacological activity of Oxtellar XR is primarily exerted through the 10-monohydroxy metabolite (MHD) of oxcarbazepine [see Clinical Pharmacology (12.3)]. The precise mechanism by which oxcarbazepine and MHD exert their antiseizure effect is unknown; however, in vitro electrophysiological studies indicate that they produce blockade of voltage-sensitive sodium channels, resulting in stabilization of hyperexcited neural membranes, inhibition of repetitive neuronal firing, and diminution of propagation of synaptic impulses. These actions are thought to be important in the prevention of seizure spread in the intact brain. In addition, increased potassium conductance and modulation of high-voltage activated calcium channels may contribute to the anticonvulsant effects of the drug. No significant interactions of oxcarbazepine or MHD with brain neurotransmitter or modulator receptor sites have been demonstrated.

12.2 Pharmacodynamics

Oxcarbazepine and its active metabolite (MHD) exhibit anticonvulsant properties in animal seizure models. They protected rodents against electrically induced tonic extension seizures and, to a lesser degree, chemically induced clonic seizures, and abolished or reduced the frequency of chronically recurring focal seizures in Rhesus monkeys with aluminum implants. No development of tolerance (i.e., attenuation of anticonvulsive activity) was observed in the maximal electroshock test when mice and rats were treated daily for five days and four weeks, respectively, with oxcarbazepine or MHD.

12.3 Pharmacokinetics

Following oral administration, oxcarbazepine is absorbed and extensively metabolized to its pharmacologically active 10-monohydroxy metabolite (MHD), which is responsible for most antiepileptic activity.

In clinical studies of Oxtellar XR, the elimination half-life of oxcarbazepine was between 7 and 11 hours; the elimination half-life of MHD is between 9 and 11 hours.

In a mass balance study in humans, only 2% of total radioactivity in plasma after administration of immediate-release oxcarbazepine was due to unchanged oxcarbazepine, with approximately 70% present as MHD, and the remainder attributable to minor metabolites.

Absorption

Oxtellar XR administered as a once daily dosage is not bioequivalent to the same total dosage of the immediate-release formulation given twice daily at steady state. Steady state plasma concentrations of MHD are reached within 5 days when Oxtellar XR is given once daily. At steady state, when 1200 mg Oxtellar XR was given once daily, MHD Cmaxoccurred 7 hours post-dose. At steady state, Oxtellar XR given once daily produced MHD exposures (AUC and Cmax) about 19% lower and MHD minimum concentrations (Cmin) about 16% lower than the immediate-release oxcarbazepine given twice daily when administered at the same 1200 mg total daily dosage. When Oxtellar XR was administered at an equivalent 600 mg single dose (4 × 150 mg tablets, 2 × 300 mg tablets, or 1 × 600 mg tablet), equivalent MHD exposures (AUC) were observed.

Following a single dose of Oxtellar XR (1 × 150 mg tablets, 1 × 300 mg tablets, or 1 × 600 mg tablet), the pharmacokinetics of MHD are not linear and show greater than dose proportional increase in AUC and less than proportional increase in Cmax: AUC increases 2.4-fold and Cmaxincreases 1.9-fold with a 2-fold increase in dose.

Effect of Food:

Single dose administration of 600 mg Oxtellar XR following a high fat meal (800 – 1000 calories) produced MHD exposure (AUC) equivalent to that produced under fasting conditions. Peak MHD concentration (Cmax) was about 60% higher and occurred 2 hours earlier under fed conditions than under fasting conditions.

The increase in Cmax, even without a significant change in the overall exposure, should be considered by the prescriber especially during the titration phase, when some adverse reactions are most likely to occur coincidentally with peak levels.

Distribution

The apparent volume of distribution of MHD is 49 L. Approximately 40% of MHD is bound to serum proteins, predominantly to albumin. Binding is independent of the serum concentration within the therapeutically relevant range. Oxcarbazepine and MHD do not bind to alpha-1-acid glycoprotein.

Elimination

Metabolism

Oxcarbazepine is rapidly reduced by cytosolic enzymes in the liver to MHD, which is primarily responsible for the pharmacological effect of Oxtellar XR®. MHD is metabolized further by conjugation with glucuronic acid. Minor amounts (4% of the dose) are oxidized to the pharmacologically inactive 10,11-dihydroxy metabolite (DHD).

Excretion

Oxcarbazepine is cleared from the body mostly in the form of metabolites which are predominantly excreted by the kidneys. More than 95% of a dose of immediate-release oxcarbazepine appears in the urine, with less than 1% as unchanged oxcarbazepine. Fecal excretion accounts for less than 4% of an administered dose. Approximately 80% of the dose is excreted in the urine either as glucuronides of MHD (49%) or as unchanged MHD (27%); the inactive DHD accounts for approximately 3% and conjugates of MHD and oxcarbazepine account for 13% of the dose.

The half-life of the parent was about two hours, while the half-life of MHD was about nine hours after the immediate-release formulation. A population pharmacokinetic model for Oxtellar XR was developed in healthy normal adults and applied to pharmacokinetic data in patients with epilepsy. For oxcarbazepine, systemic parameters were scaled allometrically, suggesting that steady state oxcarbazepine exposure will vary inversely with weight.

Specific Populations

Geriatric Patients

No studies with Oxtellar XR in elderly patients have been completed [see Use in Specific Populations (8.5)].

Following administration of single (300 mg) and multiple (600 mg/day) doses of immediate-release oxcarbazepine to elderly volunteers (60-82 years of age), the maximum plasma concentrations and AUC values of MHD were 30%-60% higher than in younger volunteers (18-32 years of age). Comparisons of creatinine clearance in young and elderly volunteers indicate that the difference was due to age-related reductions in creatinine clearance.

Pediatric Patients

A pharmacokinetic study of Oxtellar XR was performed in 18 pediatric patients with epilepsy, which included patients 6 to less than 17 years of age, after multiple doses. The population pharmacokinetic model suggested that dosing of pediatric patients with Oxtellar XR can be determined based on body weight. Weight-normalized doses in pediatric patients should produce MHD exposures (AUC) comparable to that in typical adults, with oxcarbazepine exposures ~40% higher in children than in adults [see Use in Specific Populations (8.4)]. The pharmacokinetics of Oxtellar XR in pediatric patients are similar when used as monotherapy or as adjunctive therapy for the treatment of partial-onset seizures.

Pediatric Patients with Obesity

A population PK analysis of immediate-release oxcarbazepine was conducted that included n=54 obese and non-obese pediatric patients 6 to <18 years of age to evaluate the potential impact of obesity on plasma oxcarbazepine exposures. Obesity was defined as BMI ≥95th percentile for age and sex based on CDC 2000 growth chart recommendations. Simulated results from this analysis suggested that the target maintenance doses for oxcarbazepine, applied in pediatric patients ≥6 years of age, produced equivalent steady-state exposure of MHD between pediatric patients with and without obesity. This finding is consistent when using total body weight, or when using fat-free mass in the simulations. Dosage adjustment according to obesity status is not necessary.

Male and Female Patients

The effects of gender have not been studied for Oxtellar XR.

No gender-related pharmacokinetic differences have been observed in children, adults, or the elderly with immediate-release oxcarbazepine.

Racial or Ethnic Groups

The effects of race have not been studied for Oxtellar XR.

Patients with Renal or Hepatic Impairment

The effects of renal or hepatic impairment have not been studied for Oxtellar XR [see Use in Specific Populations (8.6, 8.7)] .

Based on investigations with immediate-release oxcarbazepine, there is a linear correlation between creatinine clearance and the renal clearance of MHD. When immediate-release oxcarbazepine is administered as a single 300 mg dose in renally-impaired patients (creatinine clearance <30 mL/min), the elimination half-life of MHD is prolonged to 19 hours, with a two-fold increase in AUC. Dosage adjustment is recommended in these patients [see Dosage and Administration (2.3)and Use in Special Populations (8.6)] .

The pharmacokinetics and metabolism of immediate-release oxcarbazepine and MHD were evaluated in healthy volunteers and hepatically impaired subjects after a single 900 mg oral dose. Mild-to-moderate hepatic impairment did not affect the pharmacokinetics of immediate-release oxcarbazepine and MHD. The pharmacokinetics of oxcarbazepine and MHD have not been evaluated in severe hepatic impairment, and therefore it is not recommended in these patients [see Use in Specific Populations (8.7)] .

Pregnant Women

Due to physiological changes during pregnancy, MHD plasma levels may gradually decrease throughout pregnancy [see Use in Specific Populations (8.1)].

Drug Interaction Studies

In Vitro:

Oxcarbazepine can inhibit CYP2C19 and induce CYP3A4/5 with potentially important effects on plasma concentrations of other drugs. In addition, several AEDs that are cytochrome P450 inducers can decrease plasma concentrations of oxcarbazepine and MHD.

Oxcarbazepine was evaluated in human liver microsomes to determine its capacity to inhibit the major cytochrome P450 enzymes responsible for the metabolism of other drugs. Results demonstrate that oxcarbazepine and its pharmacologically active 10-monohydroxy metabolite (MHD) have little or no capacity to function as inhibitors for most of the human cytochrome P450 enzymes evaluated (CYP1A2, CYP2A6, CYP2C9, CYP2D6, CYP2E1, CYP4A9 and CYP4A11) with the exception of CYP2C19 and CYP3A4/5.

Although inhibition of CYP3A4/5 by oxcarbazepine and MHD did occur at high concentrations, it is not likely to be of clinical significance. The inhibition of CYP2C19 by oxcarbazepine and MHD, is clinically relevant.

In vitro, the UDP-glucuronyl transferase level was increased, indicating induction of this enzyme. Increases of 22% with MHD and 47% with oxcarbazepine were observed. As MHD, the predominant plasma substrate, is only a weak inducer of UDP-glucuronyl transferase, it is unlikely to have an effect on drugs that are mainly eliminated by conjugation through UDP-glucuronyl transferase (e.g., valproic acid, lamotrigine).

In addition, oxcarbazepine and MHD induce a subgroup of the cytochrome P450 3A family (CYP3A4 and CYP3A5) responsible for the metabolism of dihydropyridine calcium antagonists, oral contraceptives and cyclosporine resulting in a lower plasma concentration of these drugs.

Several AEDs that are cytochrome P450 inducers can decrease plasma concentrations of oxcarbazepine and MHD. No autoinduction has been observed with immediate-release oxcarbazepine.

As binding of MHD to plasma proteins is low (40%), clinically significant interactions with other drugs through competition for protein binding sites are unlikely.

In Vivo:

Other Antiepileptic Drugs

Potential interactions between immediate-release oxcarbazepine and other AEDs were assessed in clinical studies. The effect of these interactions on mean AUCs and Cmin are summarized in Table 5 [see Drug Interactions (7.1, 7.2)].

Table 5: AED Drug Interactions with Immediate-Release (IR) Oxcarbazepine
AED Coadministered (daily dosage) | IR-Oxcarbazepine (daily dosage) | Influence of IR-Oxcarbazepine on AED Concentration Mean Change [90% Confidence Interval] | Influence of AED on MHD Concentration (Mean Change, 90% Confidence Interval)
Carbamazepine (400 – 2000 mg) | 900 mg | nc [nc denotes a mean change of less than 10%] | 40% decrease [CI: 17% decrease, 57% decrease]
Phenobarbital (100 – 150 mg) | 600 – 1800 mg | 14% increase [CI: 2% increase, 24% increase] | 25% decrease [CI: 12% decrease, 51% decrease]
Phenytoin (250 – 500 mg) | 600 – 1800 >1200-2400 | nc , [Pediatrics] up to 40% increase [Mean increase in adults at high doses of immediate-release oxcarbazepine] [CI: 12% increase, 60% increase] | 30% decrease [CI: 3% decrease, 48% decrease]
Valproic Acid (400 – 2800 mg) | 600-1800 | nc | 18% decrease [CI: 13% decrease, 40% decrease]
Lamotrigine (200 mg) | 1200 | nc | nc

Hormonal Contraceptives

Coadministration of immediate-release oxcarbazepine with an oral contraceptive has been shown to influence the plasma concentrations of two components of hormonal contraceptives, ethinylestradiol (EE) and levonorgestrel (LNG). The mean AUC values of EE were decreased by 48% [90% CI: 22-65] in one study and 52% [90% CI: 38-52] in another study. The mean AUC values of LNG were decreased by 32% [90% CI: 20-45] in one study and 52% [90% CI: 42-52] in another study.

Other Drug Interactions

Calcium Antagonists: After repeated coadministration of immediate-release oxcarbazepine, the AUC of felodipine was lowered by 28% [90% CI: 20-33]. Verapamil produced a decrease of 20% [90% CI: 18-27] of the plasma levels of MHD after coadministration with immediate-release oxcarbazepine

Cimetidine, erythromycin and dextropropoxyphene had no effect on the pharmacokinetics of MHD after coadministration with immediate-release oxcarbazepine. Results with warfarin show no evidence of interaction with either single or repeated doses of immediate-release oxcarbazepine.

13 NONCLINICAL TOXICOLOGY

13.1 Carcinogenesis, Mutagenesis, Impairment of Fertility

Carcinogenesis

In two-year carcinogenicity studies, oxcarbazepine was administered in the diet at doses of up to 100 mg/kg/day to mice and by gavage at doses of up to 250 mg/kg/day to rats, and the pharmacologically active 10-hydroxy metabolite (MHD) was administered orally at doses of up to 600 mg/kg/day to rats. In mice, a dose-related increase in the incidence of hepatocellular adenomas was observed at oxcarbazepine doses ≥ 70 mg/kg/day or approximately 0.1 times the maximum recommended human dose (MRHD) on a mg/m^2basis. In rats, the incidence of hepatocellular carcinomas was increased in females treated with oxcarbazepine at doses ≥25 mg/kg/day (0.1 times the MRHD on a mg/m^2basis), and incidences of hepatocellular adenomas and/or carcinomas were increased in males and females treated with MHD at doses of 600 mg/kg/day (2.4 times the MRHD on a mg/m^2basis) and ≥ 250 mg/kg/day (equivalent to the MRHD on a mg/m^2basis), respectively. There was an increase in the incidence of benign testicular interstitial cell tumors in rats at 250 mg oxcarbazepine/kg/day and at ≥ 250 mg MHD/kg/day, and an increase in the incidence of granular cell tumors in the cervix and vagina in rats at 600 mg MHD/kg/day.

Mutagenesis

Oxcarbazepine increased mutation frequencies in the Ames test in vitro in the absence of metabolic activation in one of five bacterial strains. Both oxcarbazepine and MHD produced increases in chromosomal aberrations and polyploidy in the Chinese hamster ovary assay in vitro in the absence of metabolic activation. MHD was negative in the Ames test, and no mutagenic or clastogenic activity was found with either oxcarbazepine or MHD in V79 Chinese hamster cells in vitro. Oxcarbazepine and MHD were both negative for clastogenic or aneugenic effects (micronucleus formation) in an in vivo rat bone marrow assay.

Impairment of Fertility

In a fertility study in which rats were administered MHD (50, 150, or 450 mg/kg) orally prior to and during mating and early gestation, estrous cyclicity was disrupted and numbers of corpora lutea, implantations, and live embryos were reduced in females receiving the highest dose (approximately two times the MRHD on a mg/m^2basis).

14 CLINICAL STUDIES

Oxtellar XR has been evaluated as adjunctive therapy for partial-onset seizures in adults. The use of Oxtellar XR for the treatment of partial-onset seizures in pediatric patients 6 years of age and older is based on adequate and well-controlled studies of Oxtellar XR in adults, along with clinical trials of immediate-release oxcarbazepine in pediatric patients, and on pharmacokinetic evaluations of the use of Oxtellar XR in pediatric patients.

14.1 Oxtellar XR Primary Trial

A multicenter, randomized, double-blind, placebo-controlled, three-arm, parallel-group study (Study 1) in male and female adults with refractory partial-onset seizures (18 to 65 years of age, inclusive) was performed to examine the safety and efficacy of Oxtellar XR.

Patients had at least three partial-onset seizures per 28 days during an 8 week Baseline Period. Subjects were receiving treatment with at least one to three antiepileptic drugs and were on stable treatment for a minimum of 4 weeks. Subjects with a diagnosis other than partial-onset seizures were excluded.

The study included an 8 week Baseline Period, followed by a Treatment Period, which included a 4 week Titration Phase followed by a 12 week Maintenance Phase. The primary endpoint of the study was median percentage change from baseline in seizure frequency per 28 days during the treatment period relative to the baseline period. The criterion for statistical significance was p<0.05. A total of 366 patients were enrolled at 88 sites in North America and Eastern Europe. Subjects were randomized to one of three treatment groups and took Oxtellar XR (1200 or 2400 mg/day) or placebo.

Table 6 presents the primary efficacy results by treatment group.

Table 6: Primary Efficacy Results in Study 1: Percent Change from Baseline in Partial-Onset Seizure Frequency in the 16-week Treatment Period
 | Median seizure frequency during 8-week baseline period (per 28 days) | Median seizure frequency during 16-week treatment period (per 28 days) | Median percent change in seizure frequency | Seizure frequency percent change effect size | P value vs placebo [Wilcoxon rank-sum test of the median percentage change in partial-onset seizure frequency per 28 days during the 16-week Treatment Phase (Titration + Maintenance Periods) relative to the 8-week Baseline Phase.]
Placebo (N=121) | 7.0 | 5.0 | -28.7 %
Oxtellar XR 1200mg/day (N=122) | 6.0 | 4.3 | -38.2 % | 9.5% | 0.078
Oxtellar XR 2400mg/day (N=123) | 6.0 | 3.7 | -42.9 % | 14.2% | 0.003

Although the 1200 mg/day-placebo contrast did not reach statistical significance, concentration-response analyses reveal that the 1200 mg/day dosage is an effective dosage.

14.2 Immediate-Release Oxcarbazepine Adjunctive Therapy Trials

The effectiveness of immediate-release oxcarbazepine as an adjunctive therapy for partial-onset seizures in adults was demonstrated at dosages of 600mg/day, 1200mg/day, and 2400mg/day (divided twice daily) in a randomized, double-blind, placebo-controlled trial. All dosages resulted in a statistically significant reduction in seizure frequency when compared to placebo (p<0.05).

The effectiveness of immediate-release oxcarbazepine in dosages of 30-46 mg/kg/day, depending on baseline weight, as an adjunctive therapy for partial-onset seizures in pediatric patients, including patients 6 to less than 17 years of age, was studied in a randomized, double-blind, placebo-controlled trial. Oxcarbazepine in the single weight-based dosage group resulted in a statistically significant reduction in seizure frequency when compared to placebo (p<0.05).

16 HOW SUPPLIED/STORAGE AND HANDLING

16.1 How Supplied

150 mg (yellow modified-oval shaped tablet printed "150" on one side with edible black ink).

Bottles of 100 tablets | NDC 17772-121-01

300 mg (brown modified-oval shaped tablet printed "300" on one side with edible black ink).

Bottles of 100 tablets | NDC 17772-122-01

600 mg (brownish red modified-oval shaped tablet printed "600" on one side with edible black ink).

Bottles of 100 tablets | NDC 17772-123-01

16.2 Storage and Handling

Store at 25°C (77°F); excursions permitted between 15°C and 30°C (59°F to 86°F) [See USP controlled room temperature]. Protect from light and moisture. Dispense in a tight, light-resistant container.

17 PATIENT COUNSELING INFORMATION

Advise the patient to read the FDA-Approved patient labeling (Medication Guide).

Administration Information

Advise patients to take the tablet whole. Do not cut, chew, or crush the tablet. Advise patients to take Oxtellar XR on an empty stomach. This means they should take Oxtellar XR at least one hour before food or at least two hours after food [see Dosage and Administration (2.1)and Clinical Pharmacology (12.3)] .

Hyponatremia

Advise patients that Oxtellar XR may reduce serum sodium concentrations especially if they are taking other medications that can lower sodium. Advise patients to report symptoms of low sodium like nausea, tiredness, lack of energy, confusion, and more frequent or more severe seizures [see Warnings and Precautions (5.1)].

Anaphylactic Reactions and Angioedema

Anaphylactic reactions and angioedema may occur during treatment with Oxtellar XR. Advise patients to immediately report signs and symptoms suggesting angioedema (swelling of the face, eyes, lips, tongue, or difficulty in swallowing or breathing) and to stop taking the drug until they have consulted with their physician [see Warnings and Precautions (5.2)].

Cross Hypersensitivity Reaction to Carbamazepine

Inform patients who have exhibited hypersensitivity reactions to carbamazepine that approximately 25%-30% of these patients may also experience hypersensitivity reactions with Oxtellar XR. If patients experience a hypersensitivity reaction while taking Oxtellar XR, advise them to consult with their physician immediately [see Warnings and Precautions (5.3)].

Serious Dermatological Reactions

Advise patients that serious skin reactions have been reported in association with immediate-release oxcarbazepine. If patients experience a skin reaction while taking Oxtellar XR, advise patients to consult with their physician immediately [see Warnings and Precautions (5.4)].

Suicidal Behavior and Ideation

Counsel patients, their caregivers, and families that AEDs, including Oxtellar XR, may increase the risk of suicidal thoughts and behavior and that they need to be alert for the emergence or worsening of symptoms of depression, any unusual changes in mood or behavior, or the emergence of suicidal thoughts, behavior, or thoughts about self-harm. Advise them to immediately report behaviors of concern to healthcare providers [see Warnings and Precautions (5.5)].

DRESS/Multi-Organ Hypersensitivity

Instruct patients that a fever associated with signs of other organ system involvement (e.g., rash, lymphadenopathy, hepatic dysfunction, etc.) occurring during treatment with Oxtellar XR may be drug-related, and advise them to consult their physician immediately [see Warnings and Precautions (5.7)].

Hematologic Reactions

Advise patients that there have been rare reports of blood disorders reported in patients treated with immediate-release oxcarbazepine. Instruct patients to immediately consult with their physician if they experience symptoms suggestive of blood disorders during treatment with Oxtellar XR [see Warnings and Precautions (5.8)].

Drug Interactions

Warn female patients of childbearing age that the concurrent use of Oxtellar XR with hormonal contraceptives may render this method of contraception less effective [see Drug Interactions (7.3)and Use in Specific Populations (8.1)]. Additional non-hormonal forms of contraception are recommended when using Oxtellar XR.

Pregnancy Registry

Advise patients to notify their healthcare provider if they become pregnant or intend to become pregnant during OXTELLAR XR therapy. Encourage patients to enroll in the North American Antiepileptic Drug (NAAED) Pregnancy Registry if they become pregnant. This registry is collecting information about the safety of antiepileptic drugs during pregnancy [see Use in Specific Populations (8.1)].

Oxtellar XR is manufactured by:

Patheon Inc.

Whitby, Ontario L1N 5Z5 CANADA

Distributed by:

Supernus Pharmaceuticals, Inc.

Rockville, MD 20850 USA

Oxtellar XR®is a trademark of Supernus Pharmaceuticals, Inc.

RA-OXT-V4

MEDICATION GUIDE
Oxtellar XR®(ahks-TEH-lahr eks ahr)
(oxcarbazepine)
extended-release tablets, for oral use

What is the most important information I should know about Oxtellar XR?
Do not stop taking Oxtellar XR without first talking to your healthcare provider. Stopping Oxtellar XR suddenly can cause serious problems.
Oxtellar XR can cause serious side effects, including:

- Oxtellar XR may cause the level of sodium in your blood to be low.Symptoms of low blood sodium include:

- nausea
- tiredness, lack of energy
- headache

- confusion
- more frequent or more severe seizures

Similar symptoms that are not related to low sodium may occur from taking Oxtellar XR. You should tell your healthcare provider if you have any of these side effects and if they bother you or they do not go away.
Some other medicines can also cause low sodium in your blood. Be sure to tell your healthcare provider about all the other medicines that you are taking.
Your healthcare provider may do blood tests to check your sodium levels during your treatment with Oxtellar XR .

- Oxtellar XR may also cause allergic reactions or serious problems which may affect organs and other parts of your body like the liver or blood cells.You may or may not have a rash with these types of reactions.
  Call your healthcare provider right away if you have any of the following:

- swelling of your face, eyes, lips, or tongue
- trouble swallowing or breathing
- a skin rash
- hives
- fever, swollen glands, or sore throat that does not go away or comes and goes

- painful sores in the mouth or around your eyes
- yellowing of your skin or eyes
- unusual bruising or bleeding
- severe fatigue or weakness
- severe muscle pain
- frequent infections that do not go away

Many people who are allergic to carbamazepine are also allergic to Oxtellar XR. Tell your healthcare provider if you are allergic to carbamazepine.

- Like other antiepileptic drugs, Oxtellar XR may cause suicidal thoughts or actions in a very small number of people, about 1 in 500.
  Call your healthcare provider right away if you have any of these symptoms, especially if they are new, worse, or worry you:

- thoughts about suicide or dying
- attempts to commit suicide
- new or worse depression
- new or worse anxiety
- feeling agitated or restless
- panic attacks

- trouble sleeping (insomnia)
- new or worse irritability
- acting aggressive, being angry, or violent
- acting on dangerous impulses
- an extreme increase in activity and talking (mania)
- other unusual changes in behavior or mood

How can I watch for early symptoms of suicidal thoughts and actions?

- Pay attention to any changes, especially sudden changes, in mood, behaviors, thoughts, or feelings.
- Keep all follow-up visits with your healthcare provider as scheduled.

Call your healthcare provider between visits as needed, especially if you are worried about symptoms.

Do not stop taking Oxtellar XR without first talking to a healthcare provider.

- Stopping Oxtellar XR suddenly can cause serious problems.
- Stopping a seizure medicine suddenly in a patient who has epilepsy may cause seizures that will not stop (status epilepticus).

Suicidal thoughts or actions may be caused by things other than medicines. If you have suicidal thoughts or actions, your healthcare provider may check for other causes.

What is Oxtellar XR?
Oxtellar XR is a prescription medicine used to treat partial onset seizures in adults and children 6 years of age and older.
Oxtellar XR is not for use in children under 6 years of age.
It is not known if Oxtellar XR is safe and effective in children under 6 years of age.

Who should not take Oxtellar XR?
Do not take Oxtellar XR if you are allergic to oxcarbazepine or any of the other ingredients in Oxtellar XR, or to eslicarbazepine acetate. See the end of this Medication Guide for a complete list of ingredients in Oxtellar XR.

What should I tell my healthcare provider before taking Oxtellar XR?
Before taking Oxtellar XR, tell your healthcare provider about all your medical conditions, including if you:

- have or have had suicidal thoughts or actions, depression or mood problems.
- have liver problems.
- have kidney problems.
- are allergic to carbamazepine. Many people who are allergic to carbamazepine are also allergic to Oxtellar XR.
- use birth control medicine. Oxtellar XR may cause your birth control medicine to be less effective. Talk to your healthcare provider about the best birth control method to use.
- are pregnant or plan to become pregnant. Oxtellar XR may harm your unborn baby. Tell your healthcare provider right away if you become pregnant while taking Oxtellar XR. You and your healthcare provider will decide if you should take Oxtellar XR while you are pregnant.
  - If you become pregnant while taking Oxtellar XR, talk to your healthcare provider about registering with the North American Antiepileptic Drug (NAAED) Pregnancy Registry.
  - The purpose of this registry is to collect information about the safety of antiepileptic medicine during pregnancy. You can enroll in this registry by calling 1-888-233-2334.
- are breastfeeding or plan to breastfeed. Oxtellar XR passes into breast milk. Talk with your healthcare provider about the best way to feed your baby if you take Oxtellar XR.

Tell your healthcare provider about all the medicines you take,including prescription and over-the-counter medicines, vitamins, and herbal supplements. Taking Oxtellar XR with certain other medicines may cause side effects or affect how well they work. Do not start or stop other medicines without talking to your healthcare provider.
Especially tell your healthcare provider if you take: carbamazepine, phenobarbital, phenytoin, or birth control medicine.
Know the medicines you take. Keep a list of them and show it to your healthcare provider and pharmacist when you get a new medicine.

How should I take Oxtellar XR?

- Do not stop taking Oxtellar XR without talking to your healthcare provider. Stopping Oxtellar XR suddenly can cause serious problems, including seizures that will not stop (status epilepticus).
- Take Oxtellar XR exactly as prescribed. Your healthcare provider may change your dose. Your healthcare provider will tell you how much Oxtellar XR to take.
- Take Oxtellar XR 1 time each day.
- Take Oxtellar XR on an empty stomach. This means you should take Oxtellar XR at least 1 hour before or at least 2 hours after a meal.
- Take Oxtellar XR tablets whole with water or other liquid.
- Do not cut, crush, or chew the tablets before swallowing.
- If you take too much Oxtellar XR call your healthcare provider right away.

What are the possible side effects of Oxtellar XR?
see " What is the most important information I should know about Oxtellar XR?"
Oxtellar XR may cause other serious side effects including:seizures that can happen more often or become worse, especially in children.
The most common side effects of Oxtellar XR include:

- dizziness
- sleepiness
- headache
- balance problems

- tremors
- vomiting
- double vision
- weakness or lack of energy (asthenia)

These are not all the possible side effects of Oxtellar XR. For more information, ask your healthcare provider or pharmacist.
Tell your healthcare provider if you have any side effect that bothers you or does not go away.
Call your doctor for medical advice about side effects. You may report side effects to FDA at 1-800-FDA-1088.

How should I store Oxtellar XR?

- Store Oxtellar XR at room temperature between 68°F to 77°F (20°C and 25°C).
- Keep Oxtellar XR in a tightly closed container and out of the light.
- Keep Oxtellar XR tablets dry.

Keep Oxtellar XR and all medicines out of the reach of children.

General Information about the safe and effective use of Oxtellar XR.
Medicines are sometimes prescribed for purposes other than those listed in a Medication Guide. Do not use Oxtellar XR for a condition for which it was not prescribed. Do not give Oxtellar XR to other people, even if they have the same symptoms that you have. It may harm them.
You can ask your healthcare provider or pharmacist for information about Oxtellar XR that is written for health professionals.

What are the ingredients in Oxtellar XR?
Active ingredient: oxcarbazepine
Inactive ingredients:
150 mg tablets: colloidal silicon dioxide, hypromellose, yellow iron oxide, magnesium stearate, methacrylic acid copolymer, microcrystalline cellulose, polyethylene glycol, polyvinyl alcohol, povidone, sodium lauryl sulfate, talc, and titanium dioxide.
300 mg tablets:colloidal silicon dioxide, hypromellose, yellow iron oxide, red iron oxide, black iron oxide, magnesium stearate, methacrylic acid copolymer, microcrystalline cellulose, polyethylene glycol, polyvinyl alcohol, povidone, sodium lauryl sulfate, talc, and titanium dioxide.
600 mg tablets:colloidal silicon dioxide, hypromellose, red iron oxide, magnesium stearate, methacrylic acid copolymer, microcrystalline cellulose, polyethylene glycol, polyvinyl alcohol, povidone, sodium lauryl sulfate, talc, and titanium dioxide.
Distributed by:
Supernus Pharmaceuticals, Inc.
© Supernus Pharmaceuticals Inc.
RA-OXT-V2
For more information, go to www.supernus.com or call 1-866-398-0833.

This Medication Guide has been approved by the U.S. Food and Drug Administration

Revised: 12/2018

PRINCIPAL DISPLAY PANEL - 150 mg Tablet Bottle Label

100 tablets
NDC 17772-121-01

Oxtellar XR™
(oxcarbazepine) extended-release tablets

Once daily.
Swallow whole. Do not cut, crush, or chew.

ATTENTION PHARMACIST:
Dispense the Accompanying
Medication Guide to
Each Patient

150 mg

Rx only

Supernus®

PRINCIPAL DISPLAY PANEL - 300 mg Tablet Bottle Label

100 tablets
NDC 17772-122-01

Oxtellar XR™
(oxcarbazepine) extended-release tablets

Once daily.
Swallow whole. Do not cut, crush, or chew.

ATTENTION PHARMACIST:
Dispense the Accompanying
Medication Guide to
Each Patient

300 mg

Supernus®

Rx only

PRINCIPAL DISPLAY PANEL - 600 mg Tablet Bottle Label

100 tablets
NDC 17772-123-01

Oxtellar XR™
(oxcarbazepine) extended-release tablets

Once daily.
Swallow whole. Do not cut, crush, or chew.

ATTENTION PHARMACIST:
Dispense the Accompanying
Medication Guide to
Each Patient

600 mg

Supernus®

Rx only